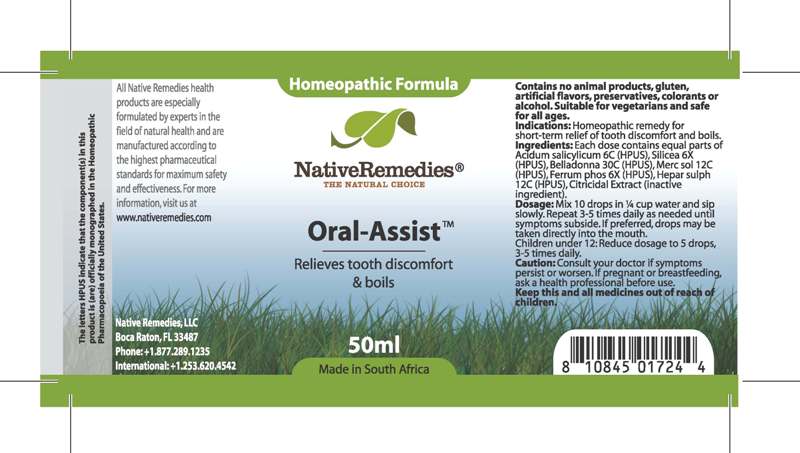 DRUG LABEL: ORAL ASSIST
NDC: 68647-172 | Form: TINCTURE
Manufacturer: Feelgood Health
Category: homeopathic | Type: HUMAN OTC DRUG LABEL
Date: 20100614

ACTIVE INGREDIENTS: SALICYLIC ACID 6 [hp_C]/33.33 mg; SILICON DIOXIDE 6 [hp_X]/33.33 mg; BELLADONNA LEAF 30 [hp_C]/33.33 mg; MERCURIUS SOLUBILIS 12 [hp_C]/33.33 mg; FERRUM PHOSPHORICUM 6 [hp_X]/33.33 mg; CALCIUM SULFIDE 12 [hp_C]/33.33 mg
INACTIVE INGREDIENTS: WATER 1 1/989.7 mg; GRAPEFRUIT SEED 1 1/0.25 mg

ORAL ASSIST

DESCRIPTION

Relieves tooth discomfort

DOSAGE AND ADMINISTRATION

Dosage: Mix 10 drops in ¼ cup water and sip slowly. Repeat 3-5 times daily as needed until symptoms subside. If preferred, drops may be taken directly into the mouth.

Children under 12: Reduce dosage to 5 drops, 3-5 times daily.

GENERAL PRECAUTIONS

Caution: Consult your doctor if symptoms persist or worsen.

Keep this and all medicines out of reach of children

ACTIVE INGREDIENT

Ingredients: Each dose contains equal parts of Acidum salicylicum 6C (HPUS), Silicea 6X (HPUS), Belladonna 30C (HPUS), Merc sol 12C (HPUS), Ferrum phos 6X (HPUS), Hepar sulph 12C (HPUS),

Citricidal Extract (inactive ingredient).

PREGNANCY

If pregnant or breastfeeding, ask a health professional before use.

USER SAFETY WARNINGS

Contains no animal products, gluten, artificial flavors, preservatives, colorants or alcohol. Suitable for vegetarians and safe for all ages

PATIENT COUNSELING INFORMATION

All Native Remedies health products are especially formulated by experts in the field of natural health and are manufactured according to the highest pharmaceutical standards for maximum safety and effectiveness

The letters HPUS indicate that the component(s) in this product is (are) officially monographed in the Homeopathic Pharmacopoeia of the United States.

Distributed by

Native Remedies, LLC

6531 Park of Commerce

Blvd. Suite C-160

Boca Raton, FL 33487

Phone: +1.877.289.1235

International: +1.253.620.4542

INDICATIONS AND USAGE

Indications: Homeopathic remedy for short-term relief of tooth discomfort and boils.